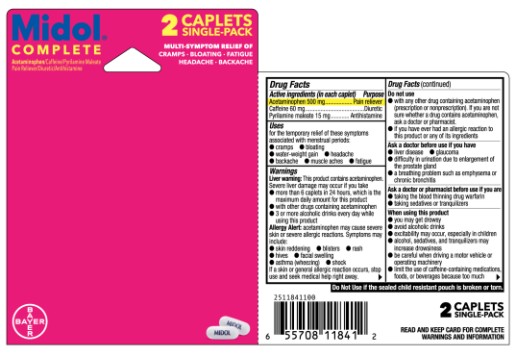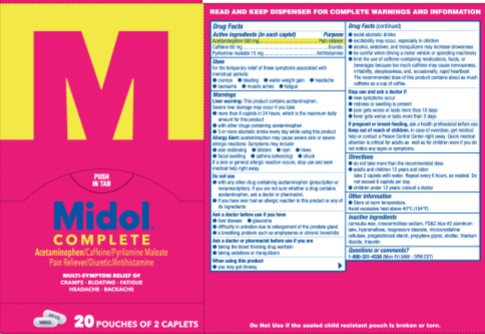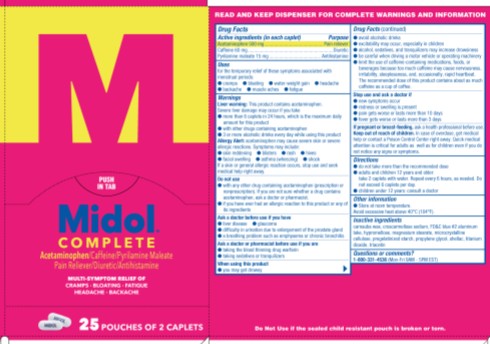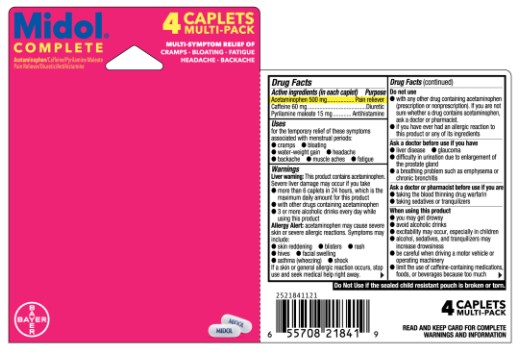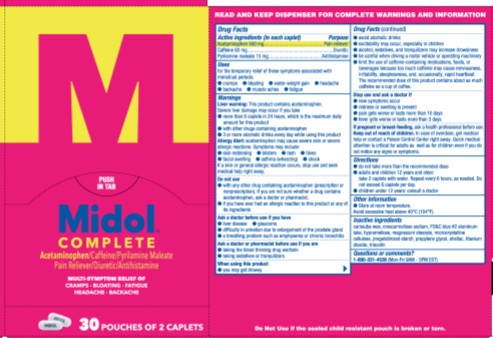 DRUG LABEL: Midol Complete
NDC: 85237-1841 | Form: TABLET
Manufacturer: Select Consumer Group
Category: otc | Type: HUMAN OTC DRUG LABEL
Date: 20251227

ACTIVE INGREDIENTS: ACETAMINOPHEN 500 mg/1 1; CAFFEINE 60 mg/1 1; PYRILAMINE MALEATE 15 mg/1 1
INACTIVE INGREDIENTS: CARNAUBA WAX; CROSCARMELLOSE SODIUM; FD&C BLUE NO. 2; HYPROMELLOSES; MAGNESIUM STEARATE; CELLULOSE, MICROCRYSTALLINE; PROPYLENE GLYCOL; SHELLAC; TITANIUM DIOXIDE; TRIACETIN

Midol®Complete

Drug Facts

ACTIVE INGREDIENT

Active ingredients (in each caplet) | Purpose
Acetaminophen 500 mg | Pain reliever
Caffeine 60 mg | Diuretic
Pyrilamine maleate 15 mg | Antihistamine

Uses

for the temporary relief of these symptoms associated with menstrual periods:

- cramps
- bloating
- water-weight gain
- headache
- backache
- muscle aches
- fatigue

Warnings

Liver warning

This product contains acetaminophen. Severe liver damage may occur if you take

- more than 6 caplets in 24 hours, which is the maximum daily amount for this product
- with other drugs containing acetaminophen
- 3 or more alcoholic drinks every day while using this product

Do not use

- with any other drug containing acetaminophen (prescription or nonprescription). If you are not sure whether a drug contains acetaminophen, ask a doctor or pharmacist.
- if you have ever had an allergic reaction to this product or any of its ingredients

Ask a doctor before use if you have

- liver disease
- glaucoma
- difficulty in urination due to enlargement of the prostate gland
- a breathing problem such as emphysema or chronic bronchitis

Ask a doctor or pharmacist before use if you are

- taking the blood thinning drug warfarin
- taking sedatives or tranquilizers

When using this product

- you may get drowsy
- avoid alcoholic drinks
- excitability may occur, especially in children
- alcohol, sedatives, and tranquilizers may increase drowsiness
- be careful when driving a motor vehicle or operating machinery
- limit the use of caffeine-containing medications, foods, or beverages because too much caffeine may cause nervousness, irritability, sleeplessness, and, occasionally, rapid heartbeat. The recommended dose of this product contains about as much caffeine as a cup of coffee.

Stop use and ask a doctor if

- new symptoms occur
- redness or swelling is present
- pain gets worse or lasts more than 10 days
- fever gets worse or lasts more than 3 days

PREGNANCY OR BREAST FEEDING

If pregnant or breast-feeding,ask a health professional before use.

Keep out of reach of children.In case of overdose, get medical help or contact a Poison Control Center right away. Quick medical attention is critical for adults as well as for children even if you do not notice any signs or symptoms.

Directions

- do not take more than the recommended dose
- adults and children 12 years and older:
  - take 2 caplets with water
  - repeat every 6 hours, as needed
  - do not exceed 6 caplets per day
- children under 12 years: consult a doctor

Other information

store at room temperature

Inactive ingredients

carnauba wax, croscarmellose sodium, FD&C blue #2 aluminum lake, hypromellose, magnesium stearate, microcrystalline cellulose, pregelatinized starch, propylene glycol, shellac, titanium dioxide, triacetin

Questions or comments?

1-800-331-4536(Mon-Fri 9AM - 5PM EST) or www.midol.com

PRINCIPAL DISPLAY PANEL - 30 pouches of 2 caplets

Midol®
Complete

Acetaminophen/Caffeine/Pyrilamine Maleate
Pain Reliever/Diuretic/Antihistamine

MAXIMUM STRENGTH
MULTI-SYMPTOM
RELIEF OF

CRAMPS, BLOATING
FATIGUE, BACKACHE
& HEADACHE

40 CAPLETS

Package / Label Principal Display 2 caplet pack

Midol ®
Complete

Acetaminophen/Caffeine/Pyrilamine Maleate
Pain Reliever/Diuretic/Antihistamine

MAXIMUM STRENGTH
MULTI-SYMPTOM
RELIEF OF

CRAMPS, BLOATING
FATIGUE, BACKACHE
& HEADACHE

2 caplet pack

Principal Package / Label display panel 4 caplets Multipack

Midol ®
Complete

Acetaminophen/Caffeine/Pyrilamine Maleate
Pain Reliever/Diuretic/Antihistamine

MAXIMUM STRENGTH
MULTI-SYMPTOM
RELIEF OF

CRAMPS, BLOATING
FATIGUE, BACKACHE
& HEADACHE

4 CAPLETS

Package / Label Principal DIsplay Panel 25 Pouches of 2 caplets

Midol ®
Complete

Acetaminophen/Caffeine/Pyrilamine Maleate
Pain Reliever/Diuretic/Antihistamine

MAXIMUM STRENGTH
MULTI-SYMPTOM
RELIEF OF

CRAMPS, BLOATING
FATIGUE, BACKACHE
& HEADACHE

25 Pouches of 2 caplets

Package / Label Principal Display Panel 20 pack of 2 caplets

Midol ®
Complete

Acetaminophen/Caffeine/Pyrilamine Maleate
Pain Reliever/Diuretic/Antihistamine

MAXIMUM STRENGTH
MULTI-SYMPTOM
RELIEF OF

CRAMPS, BLOATING
FATIGUE, BACKACHE
& HEADACHE

20 Pouches of 2 caplets